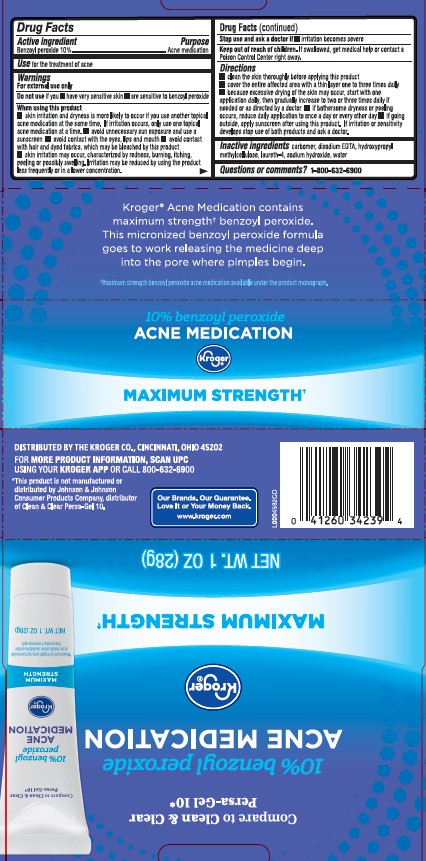 DRUG LABEL: Acne Treatment
NDC: 30142-877 | Form: GEL
Manufacturer: Kroger
Category: otc | Type: HUMAN OTC DRUG LABEL
Date: 20250715

ACTIVE INGREDIENTS: BENZOYL PEROXIDE 1 mg/1 g
INACTIVE INGREDIENTS: CARBOXYPOLYMETHYLENE; EDETATE DISODIUM ANHYDROUS; HYPROMELLOSE, UNSPECIFIED; LAURETH-4; SODIUM HYDROXIDE; WATER

Kroger 229.001/229AC-AD
10% Benzoyl Peroxide Acne Medicated Gel

Active ingredient

Benzoyl peroxide 10%

Purpose

Acne medication

Use

for the treatment of acne

Warnings

For external use only

Do not use if you

- have very sensitive skin
- are sensitive to benzoyl peroxide

When using this product

- skin irritation and dryness is more likely to occur if you use aother topical acne medication at the same time. If irritation occurs, only use one topical acne medication at a time
- avoid unnecessary sun exposure and use a sunscreen
- avoid contact with eyes, lips and mouth
- avoid contact with hair and dyed fabrics, which may be bleached by this product
- skin irritation may occur, characterized by redness, burning, itching, peeling or possible swelling. Irritation may be reduced by using the product less frequently or in a lower concentration

stop use and ask a doctor if

irritation becomes severe

Keep out of reach of children.

If swallowed, get medical help or contact a Poison Control Center right away.

Directions

- clean the skin thoroughly before applying this product
- cover the entire affected area with a thin layer one to three times daily
- because excessive drying of the skin may occur, start with one application daily, then gradually increase to two or three times daily if needed or as directed by a doctor
- if bothersome dryness or peeling occurs, reduce daily application to once a day or every other day
- if going outside, apply sunscreen after using this product. If irritation or sensitivity develops stop use of both products and ask a doctor.

inactive ingredients

carbomer, disodium EDTA, hydroxypropyl methylcellulose, laureth-4, sodium hydroxide, water

Questions or comments?

1-800-632-6900

Claims

KrogerAcne Medication contains maximum strength benzoyl peroxide.

This micronized benzoyl peroxide formula goes to work releasing the medicine deep into the pore where pimples begin.

Maximum strength benzoyl peroxide acne medication available under the product monograph.

10 % benzoyl peroxide Acne Medication

Kroger

Maximum Strength

ADVERSE REACTION

DISTRIBUTED BY THE KROGER CO. CINCINNATI, OHIO 45202

FOR MORE PRODUCT INFORMATION, SCAN UPC USING YOUR KROGER APP OR CALL 800-632-6900

Our Brands. Our Guarantee. Love it or Your Money Back.

www.kroger.com

Disclaimer

*This product is not manufactured of distributed by Johnson & Johnson Consumer Products Company, distributer of Clean & Clear Persa-Gel 10.

principal display panel

Compare to Clean & Clear Persa-Gel 10*

10% benzoyl peroxide

Acne Medication

Kroger®

Maximum Strength†

NET WT. 1 OZ (28 g)